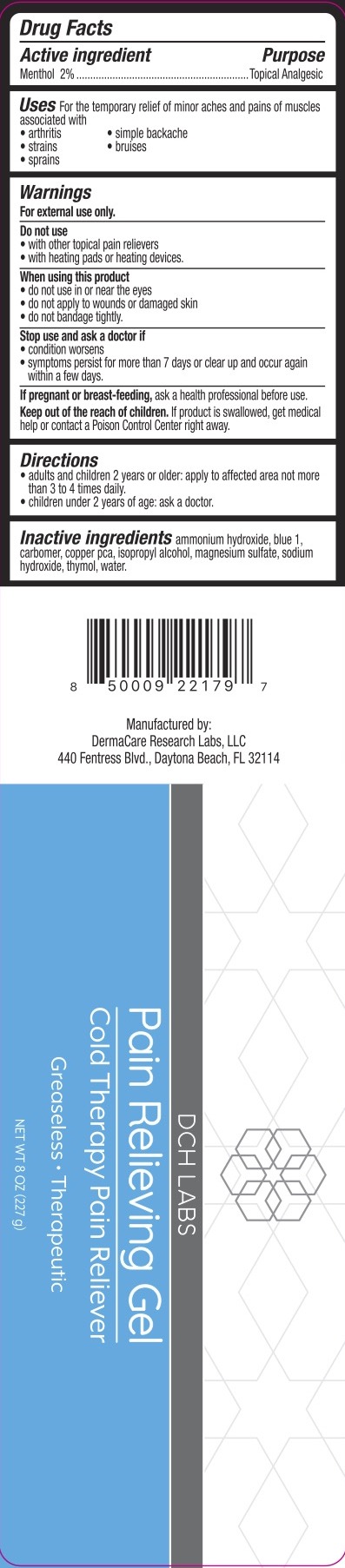 DRUG LABEL: DCH Pain Relieving
NDC: 72839-031 | Form: GEL
Manufacturer: Derma Care Research Labs, LLC
Category: otc | Type: HUMAN OTC DRUG LABEL
Date: 20241219

ACTIVE INGREDIENTS: MENTHOL 2 g/100 g
INACTIVE INGREDIENTS: AMMONIA; FD&C BLUE NO. 1; WATER; CARBOMER INTERPOLYMER TYPE B (ALLYL PENTAERYTHRITOL CROSSLINKED); COPPER PIDOLATE; PROPYLENE GLYCOL; MAGNESIUM SULFATE, UNSPECIFIED FORM; ISOPROPYL ALCOHOL; THYMOL; SODIUM HYDROXIDE

DCH Pain Relieving Gel, Menthol 2%

ACTIVE INGREDIENT

Menthol 2%

PURPOSE

Topical Analgesic

INDICATIONS AND USAGE

For the temporary relief of minor aches and pains associated with arthritis, simple backache, strains, sprains, and bruises.

WARNINGS

For external use only.

Do not use with other topical pain relievers, with heating pad or heating devices.

When using this product do not use in or near the eyes, do not apply to wounds or damaged skin, do not bandage tightly.

Stop use and ask a doctor if condition worsens, symptoms last more than 7 days or clear and occur again within a few days.

KEEP OUT OF REACH OF CHILDREN

If product is swallowed, get medical help or contact a Poison Control Center right away.

DOSAGE AND ADMINISTRATION

• adults and children 12 years and older, apply to affected area not more than 3 to 4 times daily. • Children under 12 years old, ask a doctor

INACTIVE INGREDIENT

Ammonium hydroxide, blue 1, carbomer, copper PCA, isopropyl alcohol, magnesium sulfate, sodium hydroxide, thymol, water.